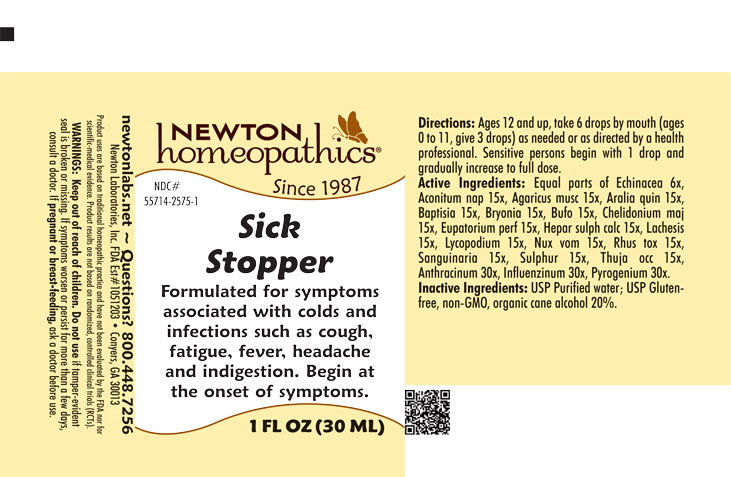 DRUG LABEL: Sick Stopper
NDC: 55714-2575 | Form: LIQUID
Manufacturer: Newton Laboratories, Inc.
Category: homeopathic | Type: HUMAN OTC DRUG LABEL
Date: 20251006

ACTIVE INGREDIENTS: ECHINACEA, UNSPECIFIED 6 [hp_X]/1 mL; AMERICAN GINSENG 15 [hp_X]/1 mL; BAPTISIA TINCTORIA ROOT 15 [hp_X]/1 mL; BRYONIA ALBA ROOT 15 [hp_X]/1 mL; CHELIDONIUM MAJUS 15 [hp_X]/1 mL; EUPATORIUM PERFOLIATUM FLOWERING TOP 15 [hp_X]/1 mL; CALCIUM SULFIDE 15 [hp_X]/1 mL; LACHESIS MUTA VENOM 15 [hp_X]/1 mL; LYCOPODIUM CLAVATUM SPORE 15 [hp_X]/1 mL; TOXICODENDRON PUBESCENS LEAF 15 [hp_X]/1 mL; SANGUINARIA CANADENSIS ROOT 15 [hp_X]/1 mL; SULFUR 15 [hp_X]/1 mL; THUJA OCCIDENTALIS LEAFY TWIG 15 [hp_X]/1 mL; BUFO BUFO CUTANEOUS GLAND 15 [hp_X]/1 mL; STRYCHNOS NUX-VOMICA SEED 15 [hp_X]/1 mL; BACILLUS ANTHRACIS IMMUNOSERUM RABBIT 30 [hp_X]/1 mL; INFLUENZA A VIRUS 30 [hp_X]/1 mL; INFLUENZA B VIRUS 30 [hp_X]/1 mL; RANCID BEEF 30 [hp_X]/1 mL; ACONITUM NAPELLUS 15 [hp_X]/1 mL; AMANITA MUSCARIA FRUITING BODY 15 [hp_X]/1 mL
INACTIVE INGREDIENTS: WATER; ALCOHOL

Sick 2575L

INDICATIONS & USAGE SECTION

Formulated for symptoms associated with colds and infections such as cough, fatigue, fever, headache and indigestion. Begin at the onset of symptoms.

OTC - ACTIVE INGREDIENT SECTION

Equal parts of Echinacea 6x, Aconitum napellus 15x, Agaricus muscarius 15x, Aralia quinquefolia 15x, Baptisia tinctoria 15x, Bryonia 15x, Bufo rana 15x, Chelidonium majus 15x, Eupatorium perfoliatum 15x, Hepar sulphuris calcareum 15x, Lachesis mutus 15x, Lycopodium clavatum 15x, Nux vom. 15x, Rhus toxicodendron 15x, Sanguinaria canadensis 15x, Sulphur 15x, Thuja occidentalis 15x, Anthracinum 30x, Influenzinum 30x, Pyrogenium 30x.

OTC - PURPOSE SECTION

Formulated for symptoms associated with colds and infections such as cough, fatigue, fever, headache and indigestion. Begin at the onset of symptoms.

INACTIVE INGREDIENT SECTION

USP Purified Water; USP Gluten-free, non-GMO, organic cane alcohol 20%.

QUESTIONS SECTION

newtonlabs.net – Questions? 800.448.7256

Newton Laboratories, Inc. FDA Est # 1051203 - Conyers, GA 30013

WARNINGS SECTION

WARNINGS: Keep out of reach of children. Do not use if tamper-evident seal is broken or missing. If symptoms worsen or persist for more than a few days, consult a doctor. If pregnant or breast-feeding, ask a doctor before use.

OTC - PREGNANCY OR BREAST FEEDING SECTION

If pregnant or breast-feeding, ask a doctor before use.

OTC - KEEP OUT OF REACH OF CHILDREN SECTION

Keep out of reach of children.

DOSAGE & ADMINISTRATION SECTION

Directions: Ages 12 and up, take 6 drops by mouth (ages 0 to 11, give 3 drops) as need or as directed by a health professional. Sensitive person begin with 1 drop and gradually increase to full dose.